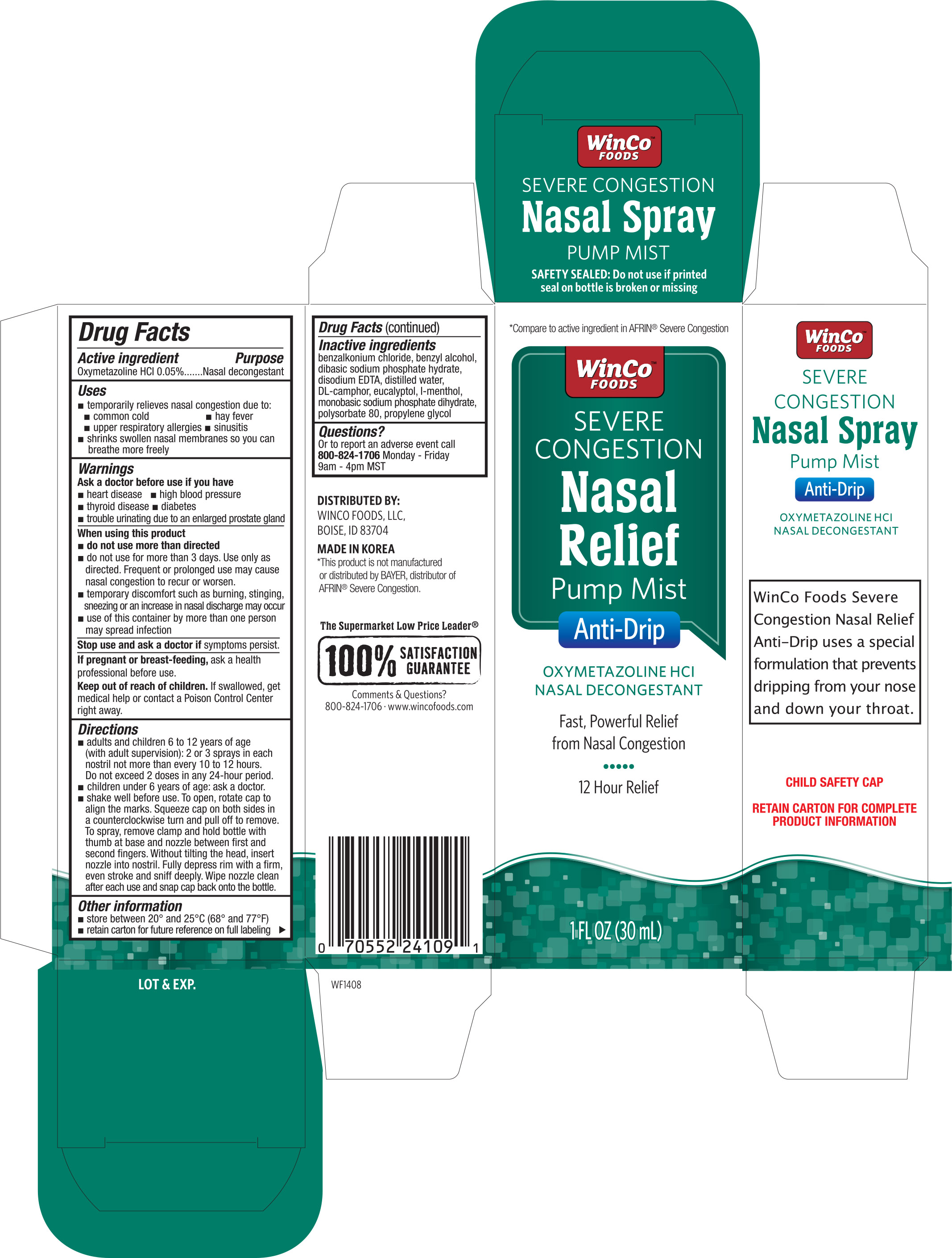 DRUG LABEL: WinCo Foods Severe Congestion Nasal Relief
NDC: 67091-192 | Form: SPRAY
Manufacturer: WinCo Foods, LLC
Category: otc | Type: HUMAN OTC DRUG LABEL
Date: 20161102

ACTIVE INGREDIENTS: OXYMETAZOLINE HYDROCHLORIDE .05 g/100 mL
INACTIVE INGREDIENTS: BENZALKONIUM CHLORIDE; BENZYL ALCOHOL; SODIUM PHOSPHATE, DIBASIC; EDETATE DISODIUM; WATER; CAMPHOR (SYNTHETIC); EUCALYPTOL; MENTHOL; SODIUM PHOSPHATE, MONOBASIC, DIHYDRATE; POLYSORBATE 80; PROPYLENE GLYCOL

Active ingredient Purpose

Oxymetazoline HCL 0.05%..............................................................................Nasal decongestant

Uses

- temporarily relieves nasal congestion due to:
- common cold
- hay fever
- upper respiratory allergies
- sinusitis
- shrinks swollen nasal membranes so you can breathe more freely

Ask a doctor before use if you have

- heart disease
- high blood pressure
- thyroid disease
- diabetes
- trouble urinating due to an enlarged prostate gland.

When using this product

do not use more than directed

- do not use more than 3 days. Use only as directed. Frequent or prolonged use may cause nasal congestion to recur or worse
- temporary discomfort such as burning, stinging, sneezing or an increase in nasal discharge may occur
- use of this container by more than one person may spread infection.

Stop use and ask a doctor if symptoms persist.

PREGNANCY

If pregnant or breast-feeding, ask ahealth professional before use.

Keep out of reach of children. If swallowed, get medical help or contact a Poison Control center right away.

Directions

- adults and children 6 to 12 years of age (with adult supervision): 2 or 3 sprays in each nostril not more than every 10 to 12 hours. Do not exceed 2 doses in any 24-hour period.
- children under 6 years of age: ask a doctor.
- shake well before use. To open, rotate cap to align the marks. Squeeze cap on both sides in a counterclockwise turn and pull off to remove. To spray, remove clamp and hold bottle with thumb at base and nozzle between first and second fingers. Without tilting the head, insert nozzle into nostril. Fully depress rim with a firm, even stroke and sniff deeply. Wipe nozzle clean after each use and snap cap back onto the bottle.

Other information

- store between 20° and 25°C (68° and 77°F)
- retain carton for future reference on full labeling

Inactive ingredients

benzalkonium chloride, benzyl alcohol, dibasic sodium phosphate hydrate, disodium EDTA, distilled water, DL-camphor, eucalyptol, l-menthol, monobasic sodium phosphate dihydrate, polysorbate 80, propylene glycol

DOSAGE AND ADMINISTRATION

DISTRIBUTED BY:

WINCO FOODS, LLC

BOISE, ID 83704

MADE IN KOREA